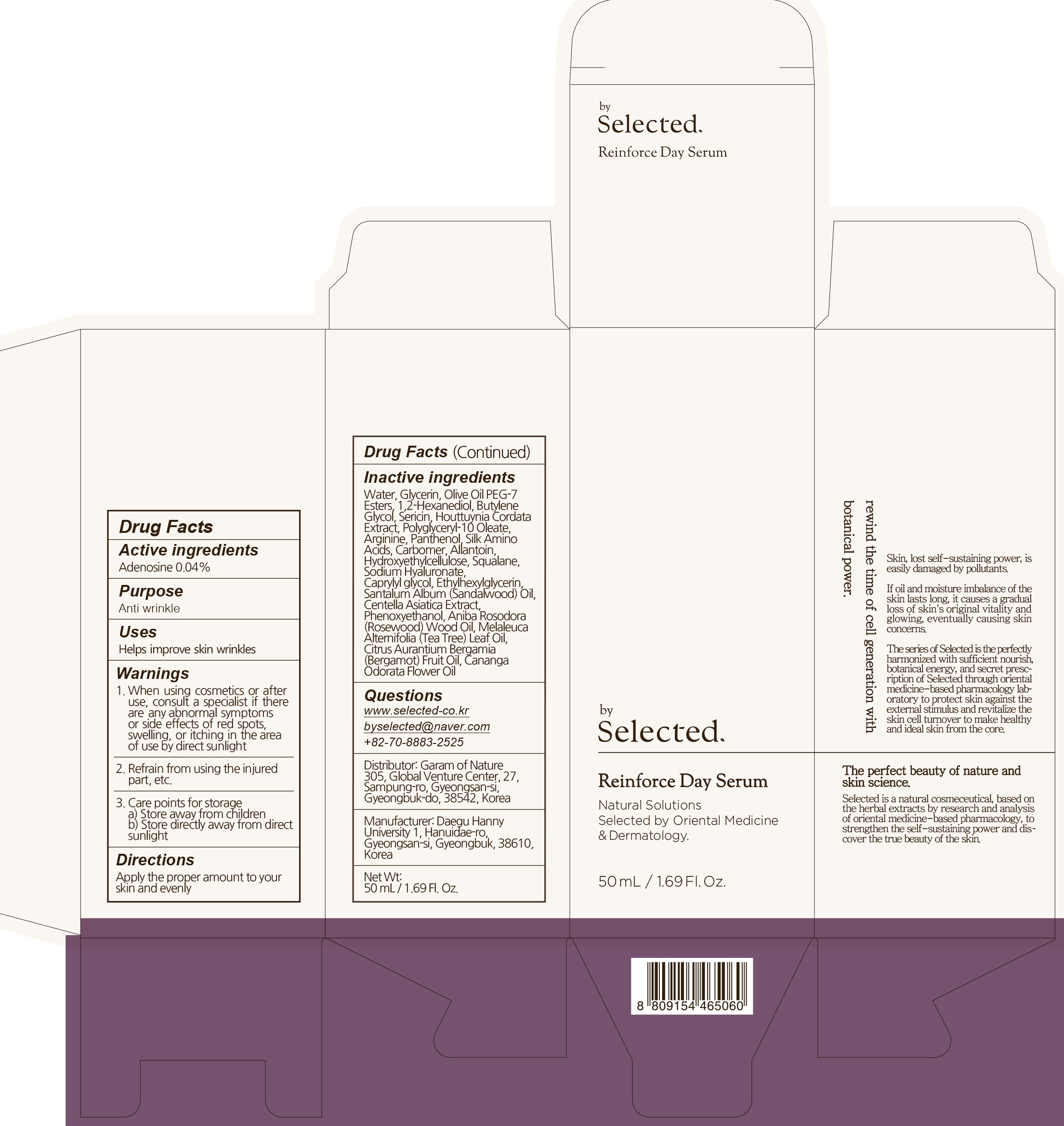 DRUG LABEL: by selected reinforce day serum
NDC: 73509-010 | Form: LIQUID
Manufacturer: Garam Of Nature
Category: otc | Type: HUMAN OTC DRUG LABEL
Date: 20191217

ACTIVE INGREDIENTS: Adenosine 0.02 g/50 mL
INACTIVE INGREDIENTS: Water; Glycerin

ACTIVE INGREDIENT

Active ingredients: Adenosine 0.04%

INACTIVE INGREDIENT

Inactive ingredients:

Water, Glycerin, Olive Oil PEG-7 Esters, 1,2-Hexanediol, Butylene Glycol, Sericin, Houttuynia Cordata Extract, Polyglyceryl-10 Oleate, Arginine, Panthenol, Silk Amino Acids, Carbomer, Allantoin, Hydroxyethylcellulose, Squalane, Sodium Hyaluronate, Caprylyl glycol, Ethylhexylglycerin, Santalum Album (Sandalwood) Oil, Centella Asiatica Extract, Phenoxyethanol, Aniba Rosodora (Rosewood) Wood Oil, Melaleuca Alternifolia (Tea Tree) Leaf Oil, Citrus Aurantium Bergamia (Bergamot) Fruit Oil, Cananga Odorata Flower Oil

PURPOSE

Purpose: Anti wrinkle

WARNINGS

1. In case of having following symptoms after using this, you're advised to stop using it immediately. If you keep using it, the symptoms will get worse and need to consult a dermatologist 1) In case of having problems such as red rash, swollenness, itching, stimulation during usage 2) In case of having the same symptoms above on the part you put this product on by direct sunlight 2. You are banned to use it on the part where you have a scar, eczema, or dermatitis 3. In case of getting it into your eyes, you have to wash it immediately 4. Caution for treatment and keeping 1) Tighten the lid after using it 2) Keep it out of infants or children's reach 3) Don't keep it in the place where the temperature is extremely hot or low and exposed to the direct sunlight

KEEP OUT OF REACH OF CHILDREN

Keep it out of infants or children's reach

Uses

Helps improve skin wrinkles

Directions

Apply the proper amount to your skin and evenly

QUESTIONS

www.selected-co.kr
byselected@naver.com
+82-70-8883-2525